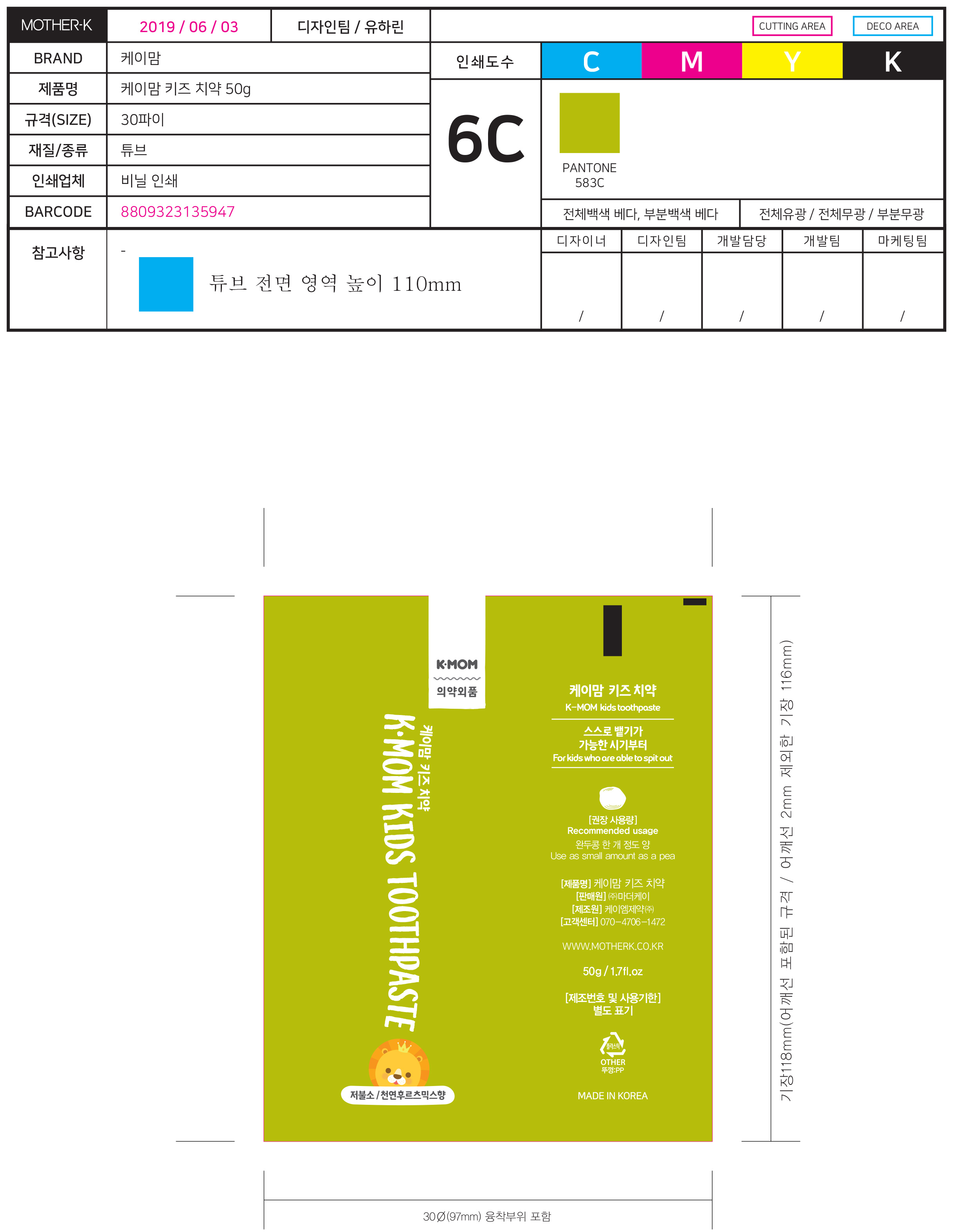 DRUG LABEL: K-MOM Kids Tooth
NDC: 73429-0001 | Form: PASTE, DENTIFRICE
Manufacturer: MOTHER-K CO.,LTD
Category: otc | Type: HUMAN OTC DRUG LABEL
Date: 20191126

ACTIVE INGREDIENTS: SILICON DIOXIDE 2 g/100 g; SODIUM MONOFLUOROPHOSPHATE 0.35 g/100 g
INACTIVE INGREDIENTS: XYLITOL; WATER

ACTIVE INGREDIENT

Silica, Sodium Monofluorosphate

PURPOSE

For dental care

Keep out of reach of children

INDICATIONS AND USAGE

Brush your teeth with a suitable amount of brush

WARNINGS

Keep out of the reach of children under 6 years of age.

If more than used for brushing is accidentally swallowed, get medical help or contact a Poison Control Center right away

INACTIVE INGREDIENT

Sorbitol, Water, Glycerin, Stevioside, Hydrated Silica, etc.

DOSAGE AND ADMINISTRATION

For dental use only